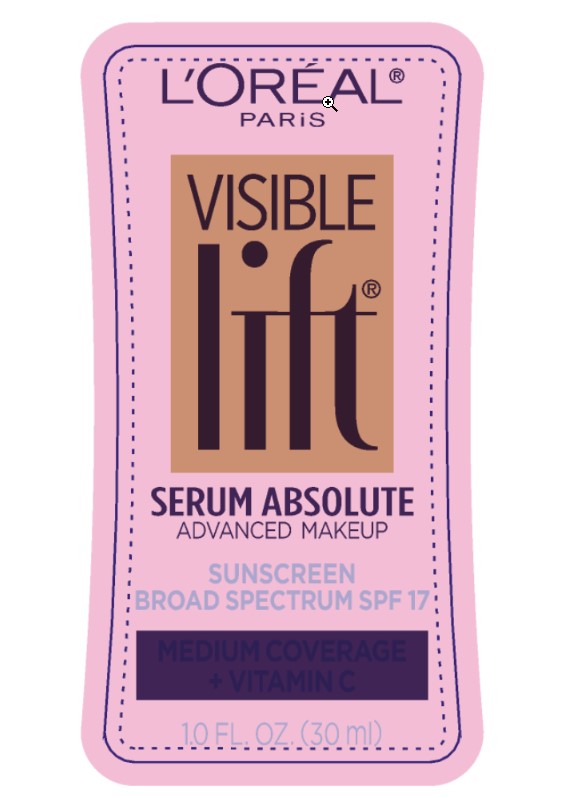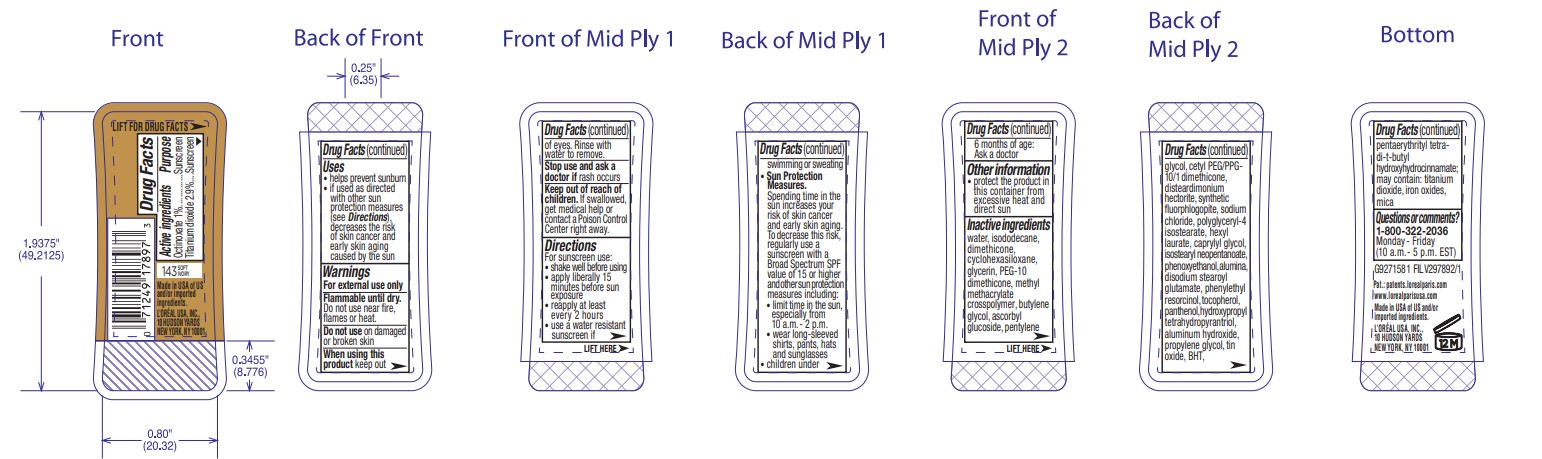 DRUG LABEL: LOreal Paris Visible Lift Serum Absolute Advanced Makeup Broad Spectrum SPF 17 Sunscreen
NDC: 49967-791 | Form: LIQUID
Manufacturer: L'Oreal USA Products Inc
Category: otc | Type: HUMAN OTC DRUG LABEL
Date: 20240627

ACTIVE INGREDIENTS: OCTINOXATE 10 mg/1 mL; TITANIUM DIOXIDE 29 mg/1 mL
INACTIVE INGREDIENTS: WATER; ISODODECANE; DIMETHICONE; CYCLOMETHICONE 6; GLYCERIN; BUTYLENE GLYCOL; ASCORBYL GLUCOSIDE; PENTYLENE GLYCOL; DISTEARDIMONIUM HECTORITE; SODIUM CHLORIDE; POLYGLYCERYL-4 ISOSTEARATE; HEXYL LAURATE; CAPRYLYL GLYCOL; ISOSTEARYL NEOPENTANOATE; PHENOXYETHANOL; ALUMINUM OXIDE; DISODIUM STEAROYL GLUTAMATE; PHENYLETHYL RESORCINOL; TOCOPHEROL; PANTHENOL; HYDROXYPROPYL TETRAHYDROPYRANTRIOL; ALUMINUM HYDROXIDE; PROPYLENE GLYCOL; STANNIC OXIDE; BUTYLATED HYDROXYTOLUENE; PENTAERYTHRITOL TETRAKIS(3-(3,5-DI-TERT-BUTYL-4-HYDROXYPHENYL)PROPIONATE); FERRIC OXIDE RED; MICA

Drug Facts

Active ingredients

Octinoxate 1%

Titanium dioxide 2.9%

Purpose

Sunscreen

Uses

- helps prevent sunburn
- if used as directed with other sun protection measures (see Directions), decreases the risk of skin cancer and early skin aging caused by the sun

Warnings

For external use only

Flammable until dry.

Do not use near fire, flames or heat.

Do not use

on damaged or broken skin

When using this product

keep out of eyes. Rinse with water to remove.

Stop use and ask a doctor if

rash occurs

Keep out of reach of children.

If swallowed, get medical help or contact a Poison Control Center right away.

Directions

For sunscreen use:

- shake well before using
- apply liberally 15 minutes before sun exposure
- reapply at least every 2 hours
- use a water resistant sunscren if swimming or sweating

Sun Protection Measures. Spending time in the sun increases our risk of skin cancer and early skin aging. To decrease this risk, regularly use a sunscreen with a Broad Spectrum SPF value of 15 or higher and other sun protection measures including:

- limit time in the sun, especially from 10 a.m. - 2 p.m.
- wear long-sleeved shirts, pants, hats, and sunglasses
- children under 6 months of age: Ask a doctor

Other information

- protect the product in this container from excessive heat and direct sun

Inactive ingredients

water, isododecane, dimethicone, cyclohexasiloxane, glycerin, PEG-10 dimethicone, methyl methacrylate crosspolymer, butylene glycol, ascorbyl glucoside, pentylene glycol, cetyl PEG/PPG-10/1 dimethicone, disteardimonium hectorite, synthetic fluorphlogopite, sodium chloride, polyglyceryl-4 isostearate, hexyl laurate, caprylyl glycol, isostearyl neopentanoate, phenoxyethanol, alumina, disodium stearoyl glutamate, phenylethyl resorcinol, tocopherol, panthenol, hydroxypropyl tetrahydropyrantriol, aluminum hydroxide, propylene glycol, tin oxide, BHT, pentaerythrityl tetra-di-t-butyl hydroxyhydrocinnamate; may contain: titanium dioxide, iron oxides, mica

Questions or comments?

1-800-322-2036

Monday - Friday

(10 a.m. - 5 p.m. EST)